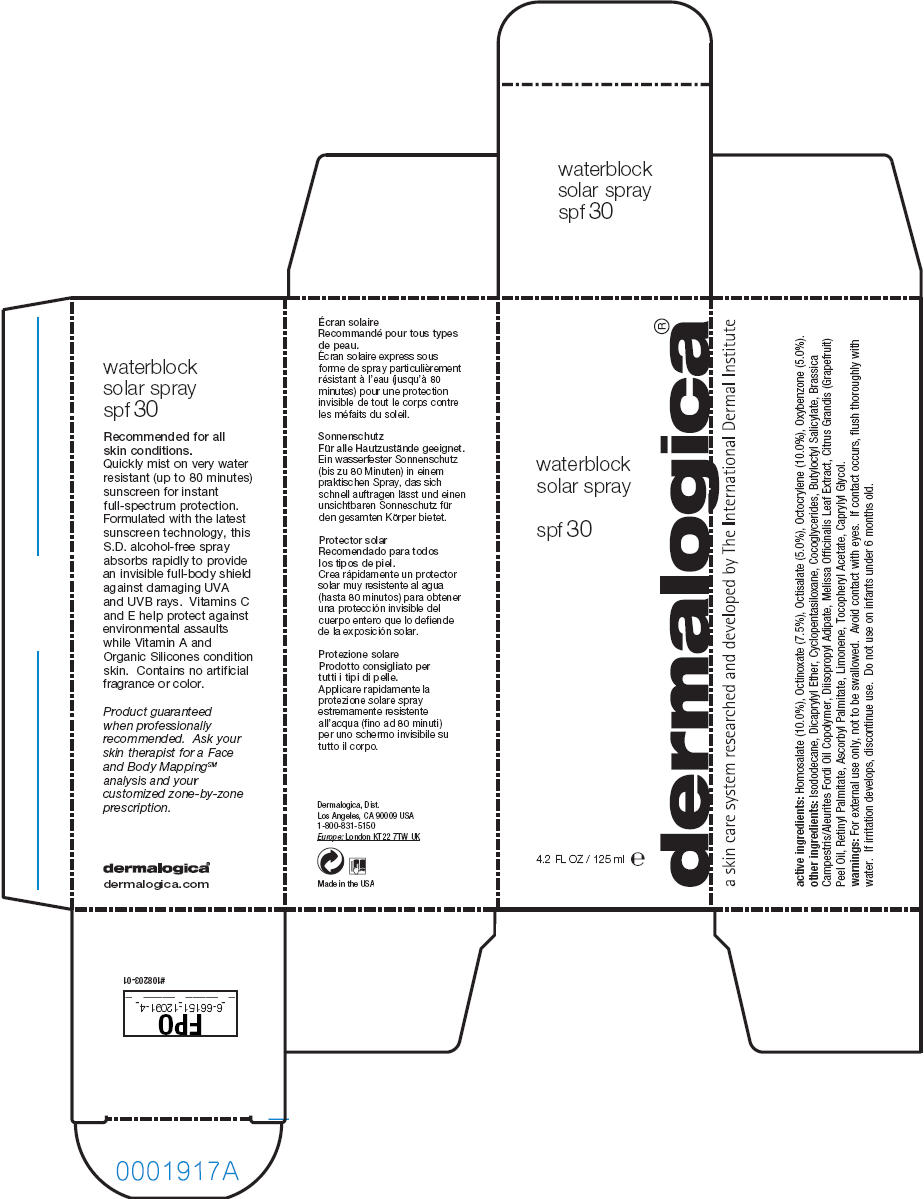 DRUG LABEL: Waterblock Solar 
NDC: 21839-091 | Form: LIQUID
Manufacturer: Gordon Laboratories, Inc
Category: otc | Type: HUMAN OTC DRUG LABEL
Date: 20111026

ACTIVE INGREDIENTS: Homosalate 12.5 mL/125 mL; Octinoxate 9.4 mL/125 mL; Octisalate 6.25 mL/125 mL; Octocrylene 12.5 mL/125 mL; Oxybenzone 6.25 mL/125 mL
INACTIVE INGREDIENTS: Isododecane; Dicaprylyl Ether; Cyclomethicone 5; Coco-glycerides; Butyloctyl Salicylate; Diisopropyl Adipate; Melissa Officinalis Leaf; Citrus Maxima Fruit Rind Oil; Vitamin A Palmitate; Ascorbyl Palmitate; Alpha-Tocopherol Acetate; Caprylyl Glycol

Dermalogica®
waterblock
solar spray
spf 30

active ingredients

Homosalate (10.0%), Octinoxate (7.5%), Octisalate (5.0%), Octocrylene (10.0%), Oxybenzone (5.0%).

other ingredients

Isododecane, Dicaprylyl Ether, Cyclopentasiloxane, Cocoglycerides, Butyloctyl Salicylate, Brassica Campestris/Aleurites Fordi Oil Copolymer, Diisopropyl Adipate, Melissa Officinalis Leaf Extract, Citrus Grandis (Grapefruit) Peel Oil, Retinyl Palmitate, Ascorbyl Palmitate, Limonene, Tocopheryl Acetate, Caprylyl Glycol.

warnings

WHEN USING

For external use only, not to be swallowed. Avoid contact with eyes. If contact occurs, flush thoroughly with water.

If irritation develops, discontinue use.

Do not use on infants under 6 months old.

Dermalogica, Dist.
Los Angeles, CA 90009 USA

PRINCIPAL DISPLAY PANEL - 125 ml Bottle Carton

waterblock
solar spray

spf 30

4.2 FL OZ / 125 ml e

dermalogica®